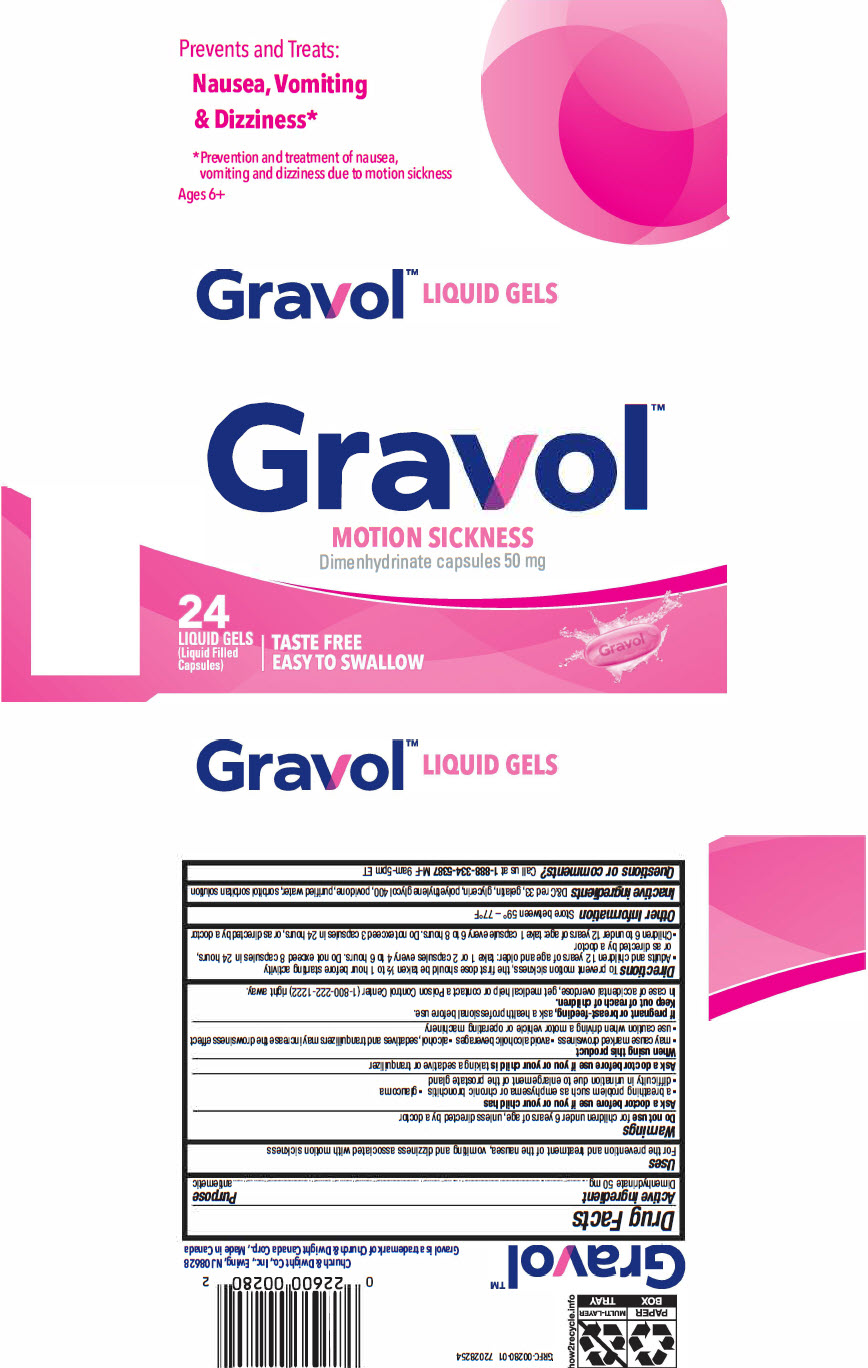 DRUG LABEL: Gravol
NDC: 10237-940 | Form: CAPSULE, LIQUID FILLED
Manufacturer: Church & Dwight Co., Inc.
Category: otc | Type: HUMAN OTC DRUG LABEL
Date: 20240513

ACTIVE INGREDIENTS: DIMENHYDRINATE 50 mg/1 1
INACTIVE INGREDIENTS: GELATIN, UNSPECIFIED; GLYCERIN; POLYETHYLENE GLYCOL 400; WATER; D&C RED NO. 33; SORBITOL; SORBITAN; POVIDONE, UNSPECIFIED

Gravol™

Drug Facts

Active ingredient

Dimenhydrinate 50 mg

Purpose

antiemetic

Uses

For the prevention and treatment of the nausea, vomiting and dizziness associated with motion sickness

Warnings

Do not use for children under 6 years of age, unless directed by a doctor

Ask a doctor before use if you or your child has

- a breathing problem such as emphysema or chronic bronchitis
- glaucoma
- difficulty in urination due to enlargement of the prostate gland

Ask a doctor before use if you or your child is taking a sedative or tranquilizer

When using this product

- may cause marked drowsiness
- avoid alcoholic beverages
- alcohol, sedatives and tranquilizers may increase the drowsiness effect
- use caution when driving a motor vehicle or operating machinery

PREGNANCY OR BREAST FEEDING

If pregnant or breast-feeding, ask a health professional before use.

Keep out of reach of children.

In case of accidental overdose, get medical help or contact a Poison Control Center (1-800-222-1222) rtght away.

Directions

To prevent motion sickness, the first dose should be taken ½ to 1 hour betore starting activity

- Adults and children 12 years of age and older: take 1 or 2 capsules every 4 to 6 hours. Do not exceed 8 capsules in 24 hours, or as directed by a doctor
- Children 6 to under 12 years of age: take 1 capsule every 6 to 8 hours. Do not exceed 3 capsules in 24 hours, or as directed by a doctor

Other Information

Store between 59° – 77°F

Inactive ingredients

D&C red 33, gelatin, glycerin, polyethylene glycol 400, povidone, purified water, sorbitol sorbitan solution

Questions or comments?

Call us at 1-888-334-5387 M-F 9am-5pm ET

PRINCIPAL DISPLAY PANEL - 50 mg Capsule Blister Pack Carton

Gravol™
MOTION SICKNESS
Dimenhydrinate capsules 50 mg

24
LIQUID GELS
(Liquid Filled
Capsules)

TASTE FREE
EASY TO SWALLOW